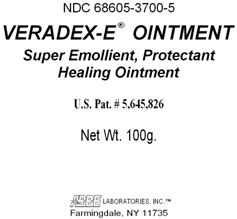 DRUG LABEL: VERADEX-E
NDC: 68605-3700 | Form: OINTMENT
Manufacturer: ABBE Laboratories, Inc.
Category: otc | Type: HUMAN OTC DRUG LABEL
Date: 20260124

ACTIVE INGREDIENTS: PETROLATUM 589.5 mg/1 g; LANOLIN 350 mg/1 g
INACTIVE INGREDIENTS: ALPHA-TOCOPHEROL ACETATE; CETYL ESTERS WAX; ETHYL METHYLPHENYLGLYCIDATE; BENZYL CINNAMATE; SALICYLIC ACID

Drug Facts

Active Ingredients
Petrolatum USP 58.95%
Anhydrous Lanolin USP 35%

Purpose
Petrolatum USP 58.95% .................................. Protectant
Anhydrous Lanolin USP 35% ....................... Protectant

INACTIVE INGREDIENT

Other ingredients: Tocopheryl Acetate, Cetyl Esters, Ethyl Methylphenylglycidate, Benzyl Cinnamate, Salicylic Acid.

Warnings: For external use only.
Discontinue use if signs of irritation appear. If condition worsens consult a doctor.
Do not use over deep, infected, or puncture wounds.

Keep from children.

INDICATIONS AND USAGE

Indications: Temporarily relieves minor burns, dry, chapped, fissured and macerated skin and lips, also relieves Psoriais, Eczema, mild sunburn, abrasions and contusions, diaper dermatitis, hemorrhoids, and prickly heat.

DOSAGE AND ADMINISTRATION

Directions: Apply a thin film to clean, dry skin three times daily. May be covered with sterile gauze, if desired.

PACKAGE LABEL

NDC 68605-3700-5

VERADEX-E® OINTMENT

Super Emollient, Protectant
Healing Ointment

Net Wt. 100g.

U.S. Pat. # 5,645,826

ABBE LABORATORIES, INC.TM
Farmingdale, NY 11735